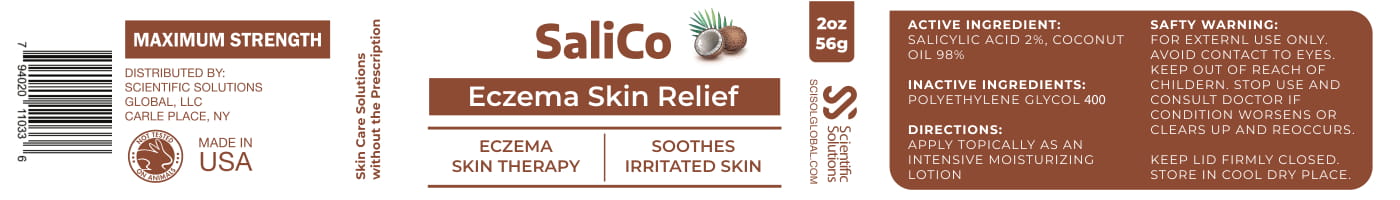 DRUG LABEL: SaliCo
NDC: 71718-304 | Form: LOTION
Manufacturer: Scientfic Solutions Global LLC
Category: otc | Type: HUMAN OTC DRUG LABEL
Date: 20191004

ACTIVE INGREDIENTS: SALICYLIC ACID 1 g/1 g
INACTIVE INGREDIENTS: COCONUT OIL; POLYETHYLENE GLYCOL 400

PACKAGE LABEL

Active Ingredient

SALICYLIC ACID 2%, COCONUT OIL 99.9%

Inactive Ingredients:

POLYETHYLENE GLYCOL 400

Directions:

APPLY TOPICALLY AS AN INTENSIVE MOISTURIZING LOTION

SAFETY WARNING:

FOR EXTERNAL USE ONLY:

AVOID CONTACT TO EYES.

KEEP OUT OF REACH OF CHILDREN.

STOP USE AND CONSULT DOCTOR IF CONDITION WORSENS OR CLEARS UP AN REOCCURS.

KEEP LID FIRMLY CLOSED.

STORE IN COOL DRY PLACE

PURPOSE

ECZEMA SKIN THERAPY

SOOTHES IRRITATED SKIN

KEEP OUT OF REACH OF CHILDREN

INDICATIONS AND USAGE

ECZEMA SKIN THERAPY

SOOTHES IRRITATED SKIN